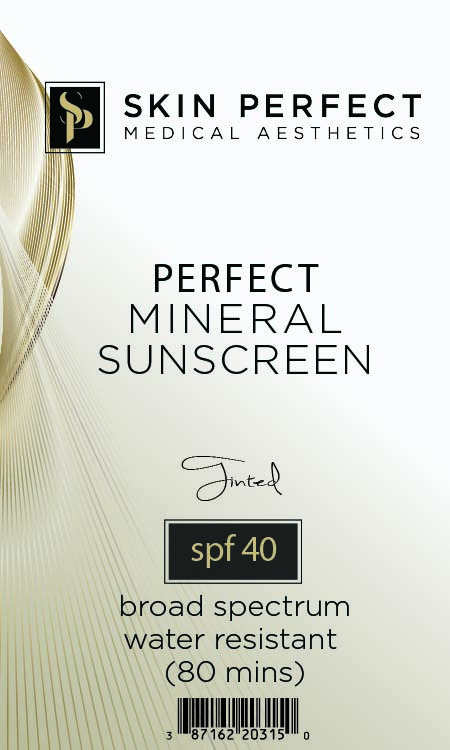 DRUG LABEL: Perfect Mineral Sunscreen
NDC: 87162-203 | Form: CREAM
Manufacturer: SKIN PERFECT MEDICAL
Category: otc | Type: HUMAN OTC DRUG LABEL
Date: 20260224

ACTIVE INGREDIENTS: TITANIUM DIOXIDE 80 mg/1 g; ZINC OXIDE 38 mg/1 g
INACTIVE INGREDIENTS: DIMETHICONE CROSSPOLYMER; CI 77491; DIMETHICONE; LAURYL PEG/PPG-18/18 METHICONE; PEG-10 DIMETHICONE (600 CST); DIMETHICONOL (2000 CST); CI 77499; TETRAHEXYLDECYL ASCORBATE; ALPHA-TOCOPHEROL ACETATE; DIMETHICONE/VINYL DIMETHICONE CROSSPOLYMER (SOFT PARTICLE); HYDROGEN DIMETHICONE (20 CST); CYCLOPENTASILOXANE; CI 77492; ALUMINA; CYCLOHEXASILOXANE

ACTIVE INGREDIENT

Titanium Dioxide 8%

Zinc Oxide 3.8%

PURPOSE

Sunscreen

INDICATIONS AND USAGE

Helps Prevent Sunburn. If used as directed with other sun protection measures (see “Directions”), decreases the risk of skin cancer and early skin aging caused by the sun.

WARNINGS

For external use only. Do not use on broken or damaged skin. Stop use and ask a doctor if rash occurs. When using this product, keep out of eyes. Rinse with water to remove. Keep out of reach of children. If swallowed, get medical help or contact a poison control center right away.

Keep out of reach of children.

DOSAGE AND ADMINISTRATION

Apply liberally 15 minutes before sun exposure. Use a water-resistant product if swimming or sweating. Reapply at least every 2 hours. Children under 6 months: Ask a doctor. Sun Protection Measures: Spending time in the sun increases your risk of skin cancer and early skin aging. To decrease this risk, regularly use a sunscreen with a Broad-Spectrum SPF value of 15 or higher and other sun protection measures including: Limit time in the sun, especially from 10 a.m. - 2 p.m. Wear long-sleeved shirts, pants, hats and sunglasses.

INACTIVE INGREDIENT

Alumina, Cyclohexasiloxane, Cyclopentasiloxane, Dimethicone, Dimethicone Crosspolymer, Dimethicone/Vinyl Dimethicone Crosspolymer, Dimethiconol, Iron Oxide (CI 77491), Lauryl PEG/PPG-18/18 Methicone, Hydrogen Dimethicone, PEG-10 Dimethicone, Tetrahexyldecyl Ascorbate, Tocopheryl Acetate

OTHER SAFETY INFORMATION

tinted

spf 40

broad spectrum

water resistant

(80 mins)